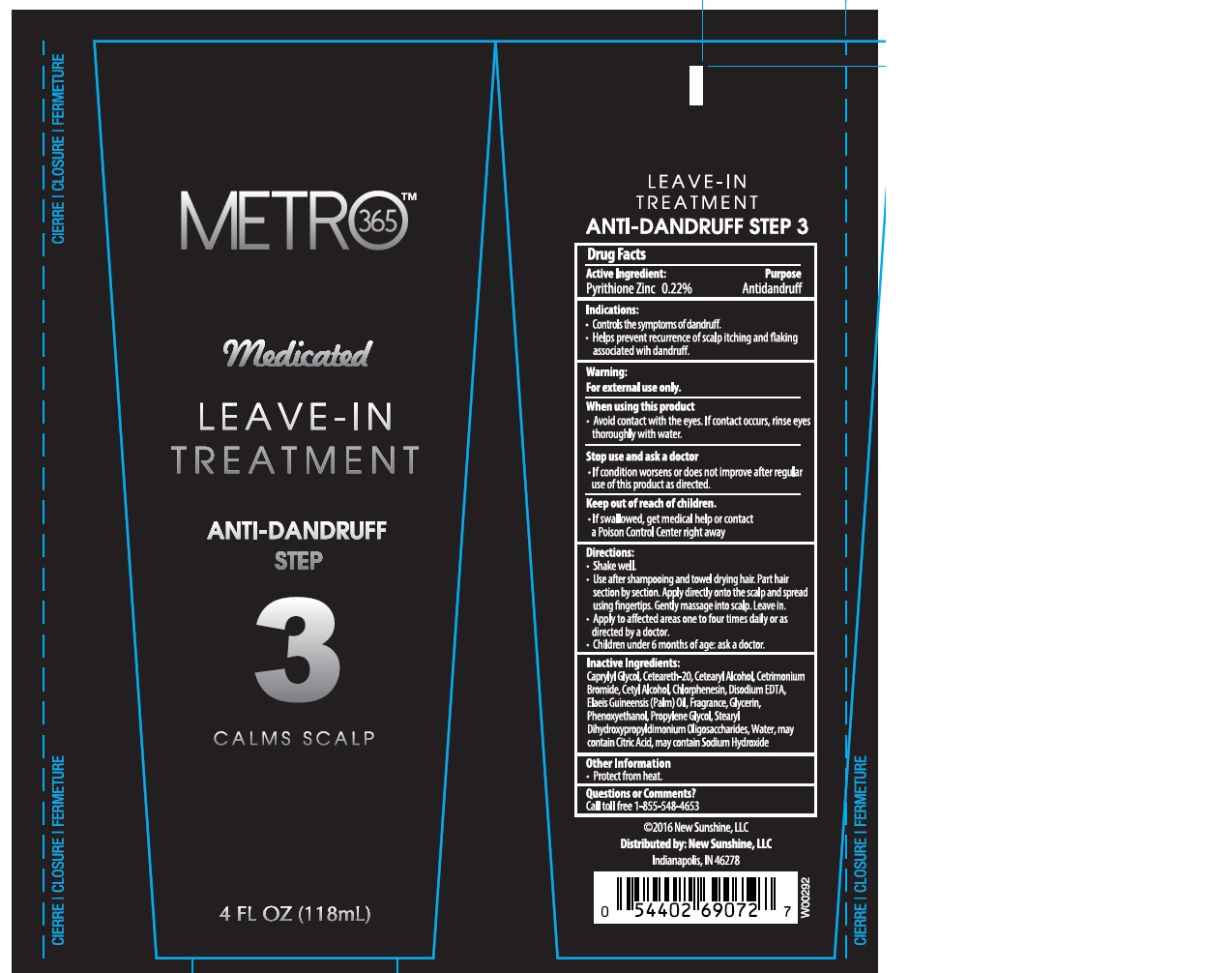 DRUG LABEL: Australian Gold
NDC: 58443-0243 | Form: CREAM
Manufacturer: Prime Enterprises Inc.
Category: otc | Type: HUMAN OTC DRUG LABEL
Date: 20200117

ACTIVE INGREDIENTS: PYRITHIONE ZINC 2.14 mg/1 mL
INACTIVE INGREDIENTS: CHLORPHENESIN; CETRIMONIUM BROMIDE; PALM OIL; EDETATE DISODIUM; GLYCERIN; PHENOXYETHANOL; SODIUM HYDROXIDE; CETYL ALCOHOL; POLYOXYL 20 CETOSTEARYL ETHER; CAPRYLYL GLYCOL; WATER; GUAR HYDROXYPROPYLTRIMONIUM CHLORIDE (1.7 SUBSTITUENTS PER SACCHARIDE); CITRIC ACID MONOHYDRATE; CETOSTEARYL ALCOHOL; PROPYLENE GLYCOL

Australian Gold Metro 365 Medicated Leave In Treatment Step 3

Active Ingredients

Pyrithione Zinc 0.22%

Purpose

Antidandruff

Indications

- Controls the symptoms of dandruff.
- Helps prevent recurrence of scalp itching and flaking associated with dandruff.

Warnings

For external use only.

When using this product

- Avoid contact with the eyes. If contact occurs, rinse eyes thouroughly with water.

Stop use and ask a doctor

- If condition worsens or does not improve after regular use of this product as directed.

Keep out of reach of children.

If swallowed, get medical help or contact a Poison Control Center right away.

Directions

- Shake well
- Use after shampooing and towel drying hair. Part hair section by section. Apply directly onto the scalp and spread using fingertips. Gently massage into scalp. Leave in.
- Apply to affected areas one to four times daily or as directed by a doctor.
- Children under 6 months of age: ask a doctor.

INACTIVE INGREDIENT

Caprylyl Glycol, Ceteareth-20, Cetearyl Alcohol, Cetrimonium Bromide, Cetyl Alcohol, Chlorphenesin, Disodium EDTA, Elaeis Guineensis (Palm) Oil, Fragrance, Glycerin, Phenoxyethanol, Propylene Glycol, Stearyl Dihydroxypropyldimonium Oligosaccharides, Water, may contain Citric Acid, may contain Sodium Hydroxide

Other Information

- Protect from heat.

Questions or Comments?

Call toll free 1-855-548-4653